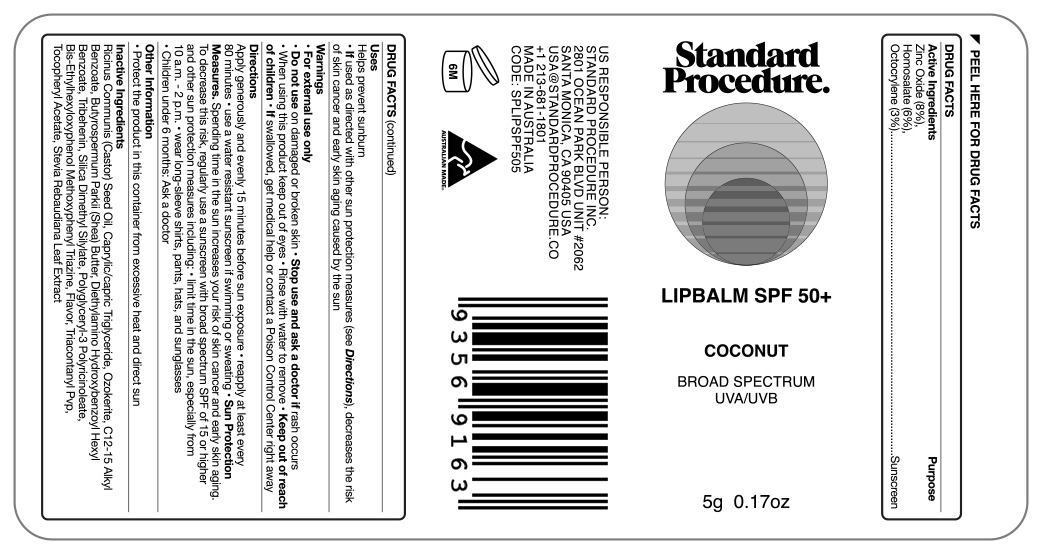 DRUG LABEL: Standard Procedure Lip Balm SPF 50
NDC: 84425-105 | Form: STICK
Manufacturer: Standard Procedure Inc
Category: otc | Type: HUMAN OTC DRUG LABEL
Date: 20260114

ACTIVE INGREDIENTS: HOMOSALATE 60 mg/1 mL; OCTOCRYLENE 30 mg/1 mL; ZINC OXIDE 80 mg/1 mL
INACTIVE INGREDIENTS: ALPHA-TOCOPHEROL ACETATE; SILICA DIMETHYL SILYLATE; TRIBEHENIN; BEMOTRIZINOL; METHYL SALICYLATE; STEVIA REBAUDIANA LEAF; POLYGLYCERYL-3 PENTARICINOLEATE; RICINUS COMMUNIS SEED; CERESIN; BUTYROSPERMUM PARKII (SHEA) BUTTER UNSAPONIFIABLES; DIETHYLAMINO HYDROXYBENZOYL HEXYL BENZOATE; TRIACONTANYL PVP (WP-660); MEDIUM-CHAIN TRIGLYCERIDES; ALKYL (C12-15) BENZOATE

Active Ingredients

Zinc Oxide 8%
Homosalate 6%
Octocrylene 3%

DOSAGE AND ADMINISTRATION

Helps prevent sunburn

If used as directed with other sun protection measures (see Directions), decrease the risk of skin cancer and early skin aging caused by the sun

Purpose

Sunscreen

Uses

Helps prevent sunbum

If used as directed with other sun protection measures (see Directions), decreases the risk of skin cancer and earty skin aging caused by the sun

Warnings

For external use only
Do not use on damaged or broken skin • Stop use and ask a doctor if rash occurs
When using this product keep out of eyes • Rinse with water to remove

Keep out of reach of children • If swallowed, get medical help or contact a Poison Control Center right away

Directions

Apply generously and evenly 15 minutes before sun exposure • reapply at least every 80 minutes • use a water resistant sunscreen if swimming or sweating

• Sun Protection Measures. Spending time in the sun increases your risk of skin cancer and early skin aging.

To decrease this risk, regularty use a sunscreen with broad spectrum SPF of 15 or higher and other sun protection measures including: • limit time in the sun, especially from 10 a.m. - 2 p.m. • wear long-sleeve shirts, pants, hats, and sunglasses

• Children under 6 months: Ask a doctor

Other Information

Protect the product in this container from excessive heat and direct sun

Inactive Ingredients

Ricinus Communis (Castor) Seed Oil, Caprylic/capric Triglyceride, Ozokerite, C12-15 Alkyl| Benzoate, Butyrospermum Parki (Shea) Butter, Diethylamino Hydroxybenzoyl Hexyl Benzoate, Tribehenin, Silica Dimethyl Silylate, Polyglyceryl-3 Polyricinoleate, Bis-Ethythexyloxyphenol Methoxypheny! Triazine, Flavor, Triacontanyl Pup,Tocopheryl Acetate, Stevia Rebaudiana Leaf

Package Label. Principal Display Panel

Standard Procedure

Lipbalm SPF 50+

Coconut

Broad Spectrum UVA/UVB

5g 0.17oz.

IMAGE Lip Balm 240410.jpg